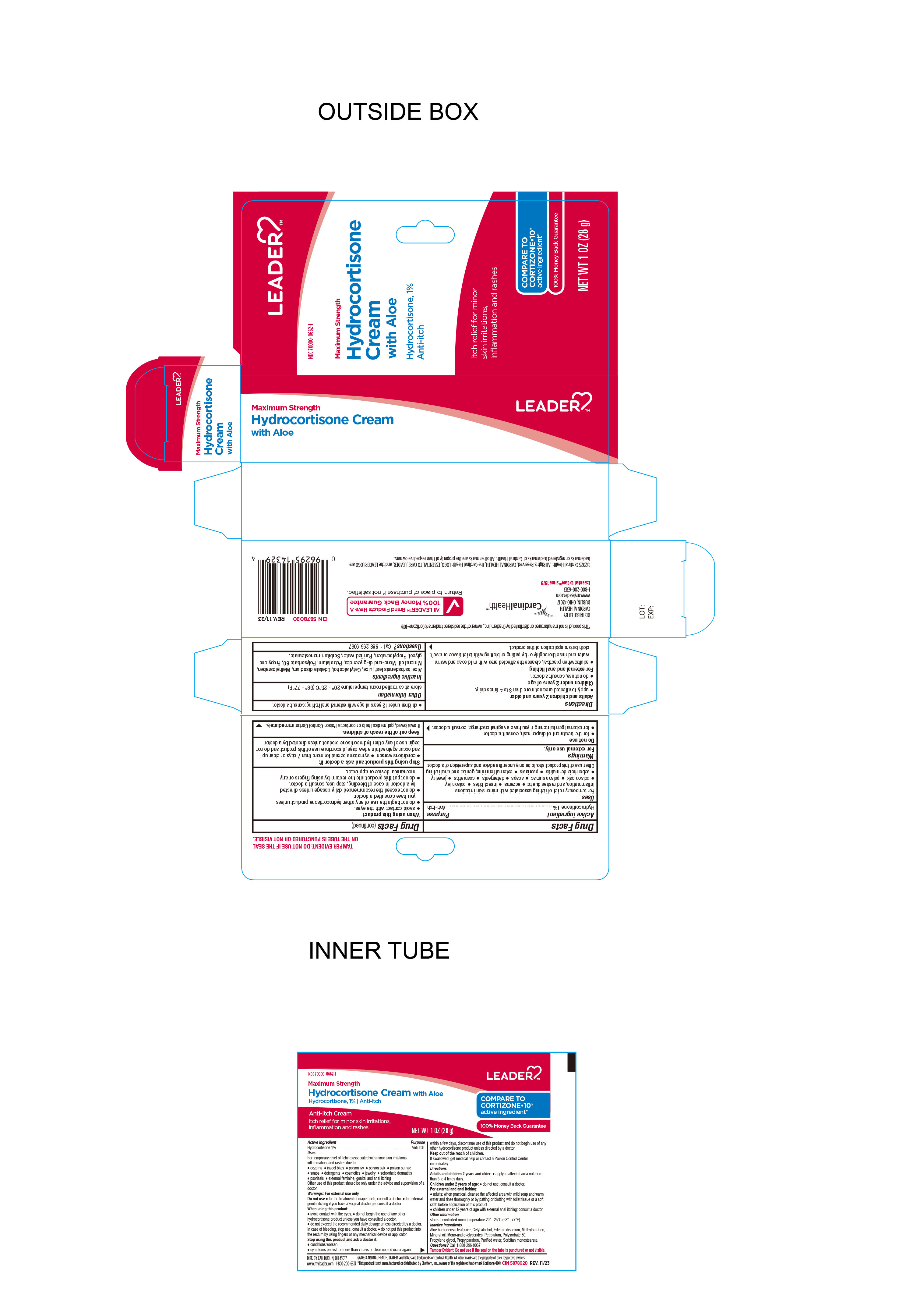 DRUG LABEL: Hydrocortisone Cream with Aloe
NDC: 70000-0662 | Form: CREAM
Manufacturer: Cardinal Health 110 dba LEADER
Category: otc | Type: HUMAN OTC DRUG LABEL
Date: 20240425

ACTIVE INGREDIENTS: HYDROCORTISONE 1 g/100 g
INACTIVE INGREDIENTS: POLYSORBATE 60; ALOE VERA LEAF; WATER; PROPYLENE GLYCOL; GLYCERYL MONO AND DIPALMITOSTEARATE; MINERAL OIL; EDETATE DISODIUM; PETROLATUM; SORBITAN MONOSTEARATE; CETYL ALCOHOL; PROPYLPARABEN; METHYLPARABEN

Leader Hydrocortisone Cream with Aloe

Active Ingredient

Hydrocortisone 1%

Purpose

Anti-Itch

Uses

For temporary relief of itching associated with minor skin irritations, inflammation, and rashes due to:

- eczema
- seborrheic dermatitis
- psoriasis
- insect bites
- poison ivy
- poison oak
- poison sumac
- soaps
- detergents
- cosmetics
- jewelry
- external feminine, genital and anal itching

Other uses of this product should be only under the advice and supervision of a doctor

Keep out of reach of children

If swallowed, get medical help or contact a Poison Control Center immediately.

Warnings

- for external use only

Stop using this product and ask a doctor

- conditions worsen
- symptoms persist for more than 7 days or clear up and occur again within a few days, discontinue use of this product and do not begin use of any other hydrocortisone product unless directed by a doctor.

Do Not Use

For the treatment of diaper rash, consult a doctor.

For external genital itching if you have a vaginal discharge, consult a doctor.

When Using this product

- Avoid contact with the eyes.
- Do not begin the use of any other hydrocortisone product unless you have consulted a doctor
- Do not exceed the recommended daily dosage unless directed by a doctor.
- In case of bleeding, stop use, consult a doctor
- Do not put this product into the rectum by using fingers or any mechanical device or applicator

Directions

Adults and children 2 years and older

apply to affected area not more than 3 to 4 times daily

Children under 2 years of age, ask a doctor

For external and anal itching

adults, when practical, cleanse the affected area with mild soap and warm water and rinse thoroughly or by patting or blotting with toilet tissue or a soft cloth before applicaiton of this product.

Inactive Ingredients

Aloe barbadensis leaf juice, cetyl alcohol, edetate disodium, methylparaben, mineral oil, mono-and-di-glycerides, petrolatum, polysorbate 60, propylene glycol, propylparaben, purified water, sorbitan monostearate.

Other Information

- store at controlled room temperature 20°-25°C (68°-77°F)
- Tamper Evident: do not use if the seal on the tube is punctured or not visible.

Other Information

Distributed By:

CARDINAL HEALTH

CAH Dublin, OH 43017

www.myleader.com

©2023 CARDINAL HEALTH. All rights reserved CARDINAL HEALTH LOGO, ESSENTIAL TO CARE, and the LEADER LOGOs are trademarks or registered trademarks of Cardinal Health. All other marks are the property of their respective owners.

1-800-200-6313

*This product is not manufactured or distributed by Chattem Inc. owner of the registered trademark Cortizone 10®

CIN 5878020

Questions

Call 1-888-296-9067